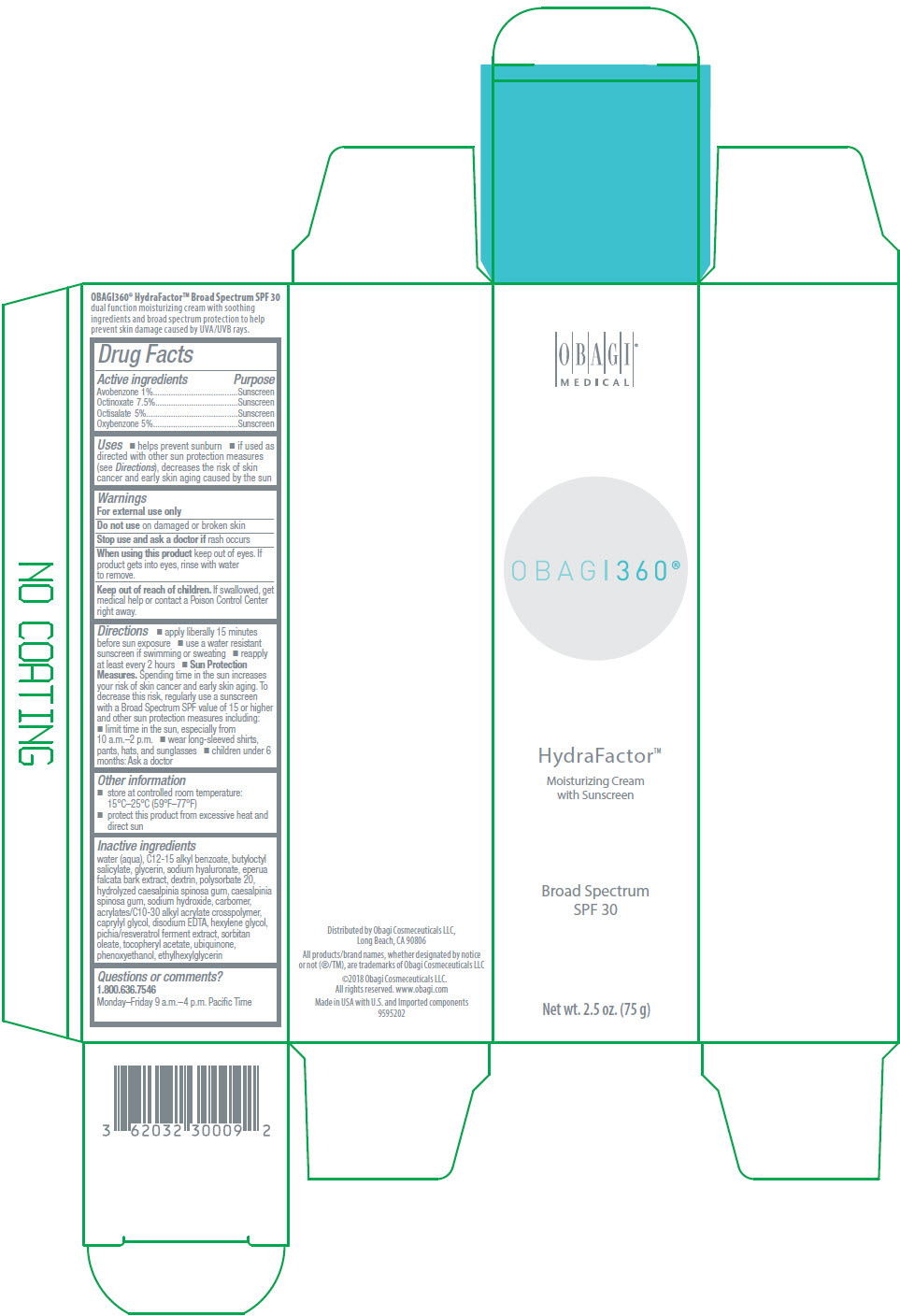 DRUG LABEL: Obagi 360 HydraFactor Moisturizing Broad Spectrum SPF 30
NDC: 62032-300 | Form: CREAM
Manufacturer: Obagi Cosmeceuticals LLC
Category: otc | Type: HUMAN OTC DRUG LABEL
Date: 20250101

ACTIVE INGREDIENTS: AVOBENZONE 10 mg/1 g; OCTINOXATE 75 mg/1 g; OCTISALATE 50 mg/1 g; OXYBENZONE 50 mg/1 g
INACTIVE INGREDIENTS: CARBOMER COPOLYMER TYPE A (ALLYL PENTAERYTHRITOL CROSSLINKED); BUTYLOCTYL SALICYLATE; ALKYL (C12-15) BENZOATE; TARA SPINOSA RESIN; CAPRYLIC ALCOHOL; CARBOMER HOMOPOLYMER TYPE C (ALLYL PENTAERYTHRITOL CROSSLINKED); ICODEXTRIN; EDETATE DISODIUM; EPERUA FALCATA BARK; ETHYLHEXYLGLYCERIN; GLYCERIN; HEXYLENE GLYCOL; PHENOXYETHANOL; POLYSORBATE 20; HYALURONATE SODIUM; SODIUM HYDROXIDE; SORBITAN MONOOLEATE; .ALPHA.-TOCOPHEROL ACETATE; UBIDECARENONE; WATER

Obagi 360® HydraFactor™ Moisturizing Cream with Sunscreen Broad Spectrum SPF 30

Drug Facts

ACTIVE INGREDIENT

Active ingredients | Purpose
Avobenzone 1% | Sunscreen
Octinoxate 7.5% | Sunscreen
Octisalate 5% | Sunscreen
Oxybenzone 5% | Sunscreen

Uses

- helps prevent sunburn
- if used as directed with other sun protection measures (see Directions), decreases the risk of skin cancer and early skin aging caused by the sun

Warnings

For external use only

Do not use on damaged or broken skin

Stop use and ask a doctor if rash occurs

When using this product keep out of eyes. If product gets into eyes, rinse with water to remove.

Keep out of reach of children. If swallowed, get medical help or contact a Poison Control Center right away.

Directions

- apply liberally 15 minutes before sun exposure
- use a water resistant sunscreen if swimming or sweating
- reapply at least every 2 hours
- Sun Protection Measures. Spending time in the sun increases your risk of skin cancer and early skin aging. To decrease this risk, regularly use a sunscreen with a Broad Spectrum SPF value of 15 or higher and other sun protection measures including:
  - limit time in the sun, especially from 10 a.m.–2 p.m.
  - wear long-sleeved shirts, pants, hats, and sunglasses
- children under 6 months: Ask a doctor

Other information

- store at controlled room temperature: 15°C–25°C (59°F–77°F)
- protect this product from excessive heat and direct sun

Inactive ingredients

water (aqua), C12-15 alkyl benzoate, butyloctyl salicylate, glycerin, sodium hyaluronate, eperua falcata bark extract, dextrin, polysorbate 20, hydrolyzed caesalpinia spinosa gum, caesalpinia spinosa gum, sodium hydroxide, carbomer, acrylates/C10-30 alkyl acrylate crosspolymer, caprylyl glycol, disodium EDTA, hexylene glycol, pichia/resveratrol ferment extract, sorbitan oleate, tocopheryl acetate, ubiquinone, phenoxyethanol, ethylhexylglycerin

Questions or comments?

1.800.636.7546

Monday–Friday 9 a.m.–4 p.m. Pacific Time

Distributed by Obagi Cosmeceuticals LLC,
Long Beach, CA 90806

PRINCIPAL DISPLAY PANEL - 75 g Tube Carton

OBAGI®
MEDICAL

OBAGI360®

HydraFactor™
Moisturizing Cream
with Sunscreen

Broad Spectrum
SPF 30

Net wt. 2.5 oz. (75 g)